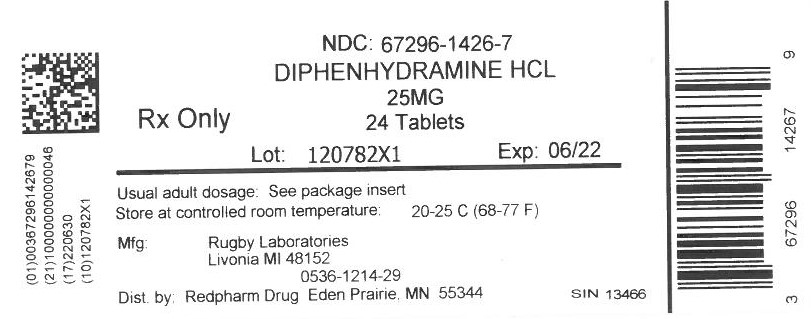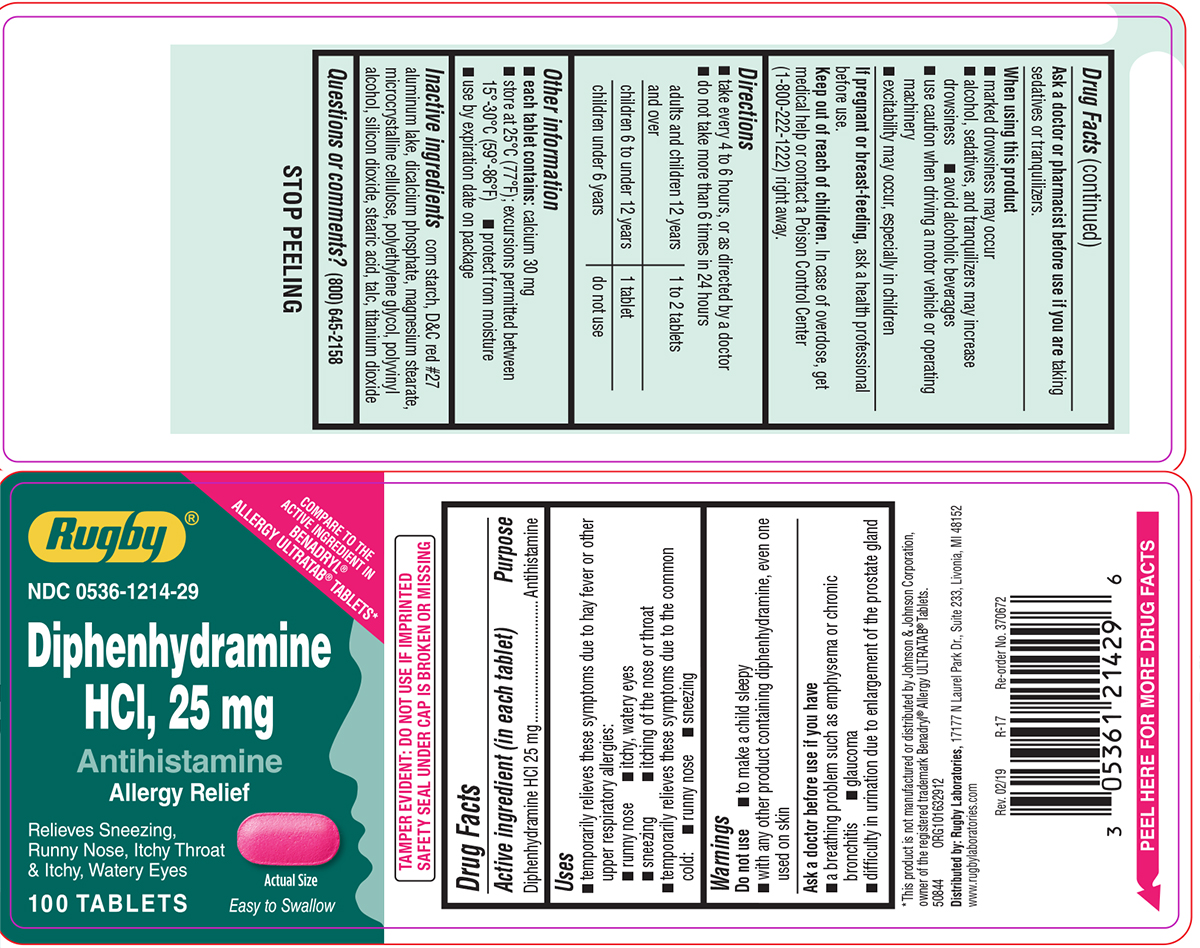 DRUG LABEL: Diphenhydramine HCl
NDC: 67296-1426 | Form: TABLET, COATED
Manufacturer: RedPharm Drug, Inc.
Category: otc | Type: HUMAN OTC DRUG LABEL
Date: 20210301

ACTIVE INGREDIENTS: DIPHENHYDRAMINE HYDROCHLORIDE 25 mg/1 1
INACTIVE INGREDIENTS: STARCH, CORN; D&C RED NO. 27; MAGNESIUM STEARATE; MICROCRYSTALLINE CELLULOSE; POLYETHYLENE GLYCOL, UNSPECIFIED; POLYVINYL ALCOHOL, UNSPECIFIED; SILICON DIOXIDE; STEARIC ACID; TALC; TITANIUM DIOXIDE; ANHYDROUS DIBASIC CALCIUM PHOSPHATE

Diphenhydramine 25mg tabs

Active ingredient (in each tablet)

Diphenhydramine HCl 25 mg

Purpose

Antihistamine

Uses

- temporarily relieves these symptoms due to hay fever or other upper respiratory allergies:
  - runny nose
  - itchy, watery eyes
  - sneezing
  - itching of the nose or throat
- temporarily relieves these symptoms due to the common cold:
  - runny nose
  - sneezing

Warnings

Do not use

- to make a child sleepy
- with any other product containing diphenhydramine, even one used on skin

Ask a doctor before use if you have

- a breathing problem such as emphysema or chronic bronchitis
- glaucoma
- difficulty in urination due to enlargement of the prostate gland

Ask a doctor or pharmacist before use if you are

taking sedatives or tranquilizers.

When using this product

- marked drowsiness may occur
- alcohol, sedatives, and tranquilizers may increase drowsiness
- avoid alcoholic beverages
- use caution when driving a motor vehicle or operating machinery
- excitability may occur, especially in children

If pregnant or breast-feeding,

ask a health professional before use.

Keep out of reach of children.

In case of overdose, get medical help or contact a Poison Control Center (1-800-222-1222) right away

Directions

- take every 4 to 6 hours, or as directed by a doctor
- do not take more than 6 times in 24 hours

adults and children 12 years and over | 1 to 2 tablets
children 6 to under 12 years | 1 tablet
children under 6 years | do not use

Other information

- each tablet contains: calcium 30 mg
- store at 25°C (77°F); excursions permitted between 15°-30°C (59°-86°F)
- protect from moisture
- use by expiration date on package

Inactive ingredients

corn starch, D&C red #27 aluminum lake, dicalcium phosphate, magnesium stearate, microcrystalline cellulose, polyethylene glycol, polyvinyl alcohol, silicon dioxide, stearic acid, talc, titanium dioxide

Questions or comments?

(800) 645-2158

Principal display panel

Rugby®

NDC 0536-1214-29

COMPARE TO THE
ACTIVE INGREDIENT IN
BENADRYL®
ALLERGY ULTRATAB® TABLETS*

Diphenhydramine HCl, 25 mg
Antihistamine
Allergy Relief

Relieves Sneezing,
Runny Nose, Itchy throat
& Itchy, Watery Eyes

100 TABLETS
Actual Size

Easy to Swallow

TAMPER EVIDENT: DO NOT USE IF IMPRINTED
SAFETY SEAL UNDER CAP IS BROKEN OR MISSING

*This product is not manufactured or distributed by Johnson & Johnson Corporation,
owner of the registered trademark Benadryl® Allergy ULTRATAB® Tablets.

50844 ORG101632912

Distributed by: Rugby Laboratories, 17177 N Laurel Park Dr., Suite 233, Livonia, MI 48152
www.rugbylaboratories.com

Rev.02/19 R-17 Re-order No. 370672